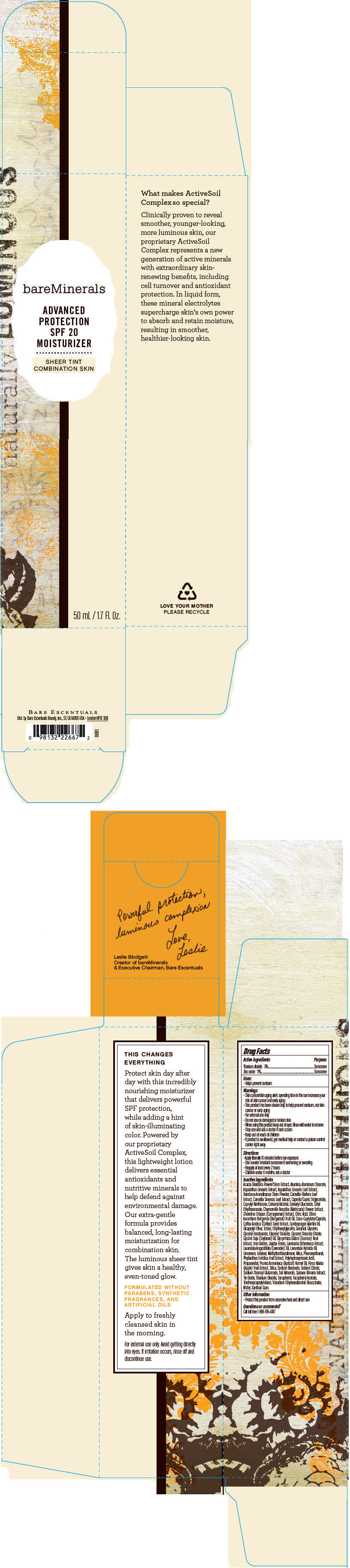 DRUG LABEL: bareMinerals Advanced Protection SPF 20 Moisturizer 
NDC: 98132-721 | Form: LOTION
Manufacturer: Bare Escentuals Beauty, Inc.
Category: otc | Type: HUMAN OTC DRUG LABEL
Date: 20140212

ACTIVE INGREDIENTS: Titanium Dioxide 50 mg/1 mL; Zinc Oxide 30 mg/1 mL
INACTIVE INGREDIENTS: ACACIA DEALBATA FLOWER; ALUMINUM OXIDE; ALUMINUM STEARATE; ASPALATHUS LINEARIS LEAF; BAMBUSA BAMBOS STEM; CAMELLIA OLEIFERA LEAF; GREEN TEA LEAF; MEDIUM-CHAIN TRIGLYCERIDES; CAPRYLYL TRISILOXANE; CETOSTEARYL ALCOHOL; CETEARYL GLUCOSIDE; CETYL ETHYLHEXANOATE; CHAMOMILE; CHONDRUS CRISPUS; CITRIC ACID MONOHYDRATE; BERGAMOT OIL; COCO-CAPRYLATE/CAPRATE; ARABICA COFFEE BEAN; PALMAROSA OIL; DICAPRYLYL ETHER; ECTOINE; ETHYLHEXYLGLYCERIN; GERANIOL; GLYCERIN; GLYCERYL ISOSTEARATE; GLYCERYL MONOSTEARATE; GLYCERYL STEARATE CITRATE; SOYBEAN OIL; GLYCYRRHIZA GLABRA; FERRIC OXIDE RED; LAMINARIA OCHROLEUCA; LAVENDER OIL; LAVANDIN OIL; LINALOOL, (+/-)-; METHYLISOTHIAZOLINONE; MICA; PHENOXYETHANOL; PHYLLANTHUS EMBLICA FRUIT; PROPANEDIOL; APRICOT KERNEL OIL; APPLE; SILICON DIOXIDE; SODIUM BENZOATE; SODIUM CITRATE; SODIUM STEAROYL GLUTAMATE; STANNIC OXIDE; TOCOPHEROL; .ALPHA.-TOCOPHEROL ACETATE; TRIETHOXYCAPRYLYLSILANE; TRISODIUM ETHYLENEDIAMINE DISUCCINATE; WATER; XANTHAN GUM

bareMinerals Advanced Protection SPF 20 Moisturizer
Sheer Tint Combination Skin

Drug Facts

ACTIVE INGREDIENT

Active ingredients | Purpose
Titanium dioxide 5% | Sunscreen
Zinc oxide 3% | Sunscreen

Uses

- Helps prevent sunburn

Warnings

- Skin cancer/skin aging alert: spending time in the sun increases your risk of skin cancer and early aging

- This product has been shown only to help prevent sunburn, not skin cancer or early aging

- For external use only

- Do not use on damaged or broken skin

- When using this product keep out of eyes. Rinse with water to remove

- Stop use and ask a doctor if rash occurs

- Keep out of reach of children

- If product is swallowed, get medical help or contact a poison control center right away

Directions

- Apply liberally 15 minutes before sun exposure
- Use a water resistant sunscreen if swimming or sweating
- Reapply at least every 2 hours
- Children under 6 months: ask a doctor

Inactive ingredients

Acacia Dealbata Flower/Stem Extract, Alumina, Aluminum Stearate, Aspalathus Linearis Extract, Aspalathus Linearis Leaf Extract, Bambusa Arundinacea Stem Powder, Camellia Oleifera Leaf Extract, Camellia Sinensis Leaf Extract, Caprylic/Capric Triglyceride, Caprylyl Methicone, Cetearyl Alcohol, Cetearyl Glucoside, Cetyl Ethylhexanoate, Chamomilla Recutita (Matricaria) Flower Extract, Chondrus Crispus (Carrageenan) Extract, Citric Acid, Citrus Aurantium Bergamia (Bergamot) Fruit Oil, Coco-Caprylate/Caprate, Coffea Arabica (Coffee) Seed Extract, Cymbopogon Martini Oil, Dicaprylyl Ether, Ectoin, Ethylhexylglycerin, Geraniol, Glycerin, Glyceryl Isostearate, Glyceryl Stearate, Glyceryl Stearate Citrate, Glycine Soja (Soybean) Oil, Glycyrrhiza Glabra (Licorice) Root Extract, Iron Oxides, Jojoba Esters, Laminaria Ochroleuca Extract, Lavandula Angustifolia (Lavender) Oil, Lavandula Hybrida Oil, Limonene, Linalool, Methylisothiazolinone, Mica, Phenoxyethanol, Phyllanthus Emblica Fruit Extract, Polyhydroxystearic Acid, Propanediol, Prunus Armeniaca (Apricot) Kernel Oil, Pyrus Malus (Apple) Fruit Extract, Silica, Sodium Benzoate, Sodium Citrate, Sodium Stearoyl Glutamate, Soil Minerals, Spiraea Ulmaria Extract, Tin Oxide, Titanium Dioxide, Tocopherol, Tocopheryl Acetate, Triethoxycaprylylsilane, Trisodium Ethylenediamine Disuccinate, Water, Xanthan Gum.

Other information

- Protect this product from excessive heat and direct sun

Questions or comments?

Call toll free 1-888-795-4747

Dist. by Bare Escentuals Beauty, Inc., SF, CA 94105 USA

PRINCIPAL DISPLAY PANEL - 50 mL Bottle Box

bareMinerals

ADVANCED
PROTECTION
SPF 20
MOISTURIZER

SHEER TINT
COMBINATION SKIN

50 mL / 1.7 Fl. Oz.